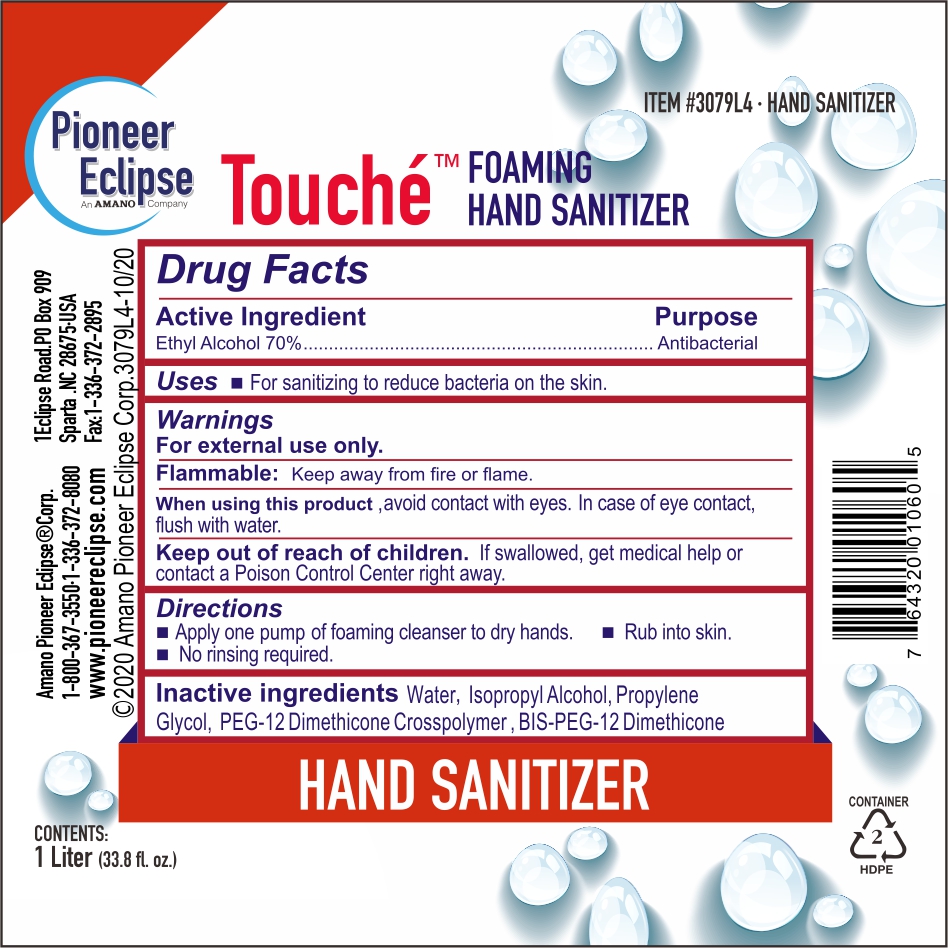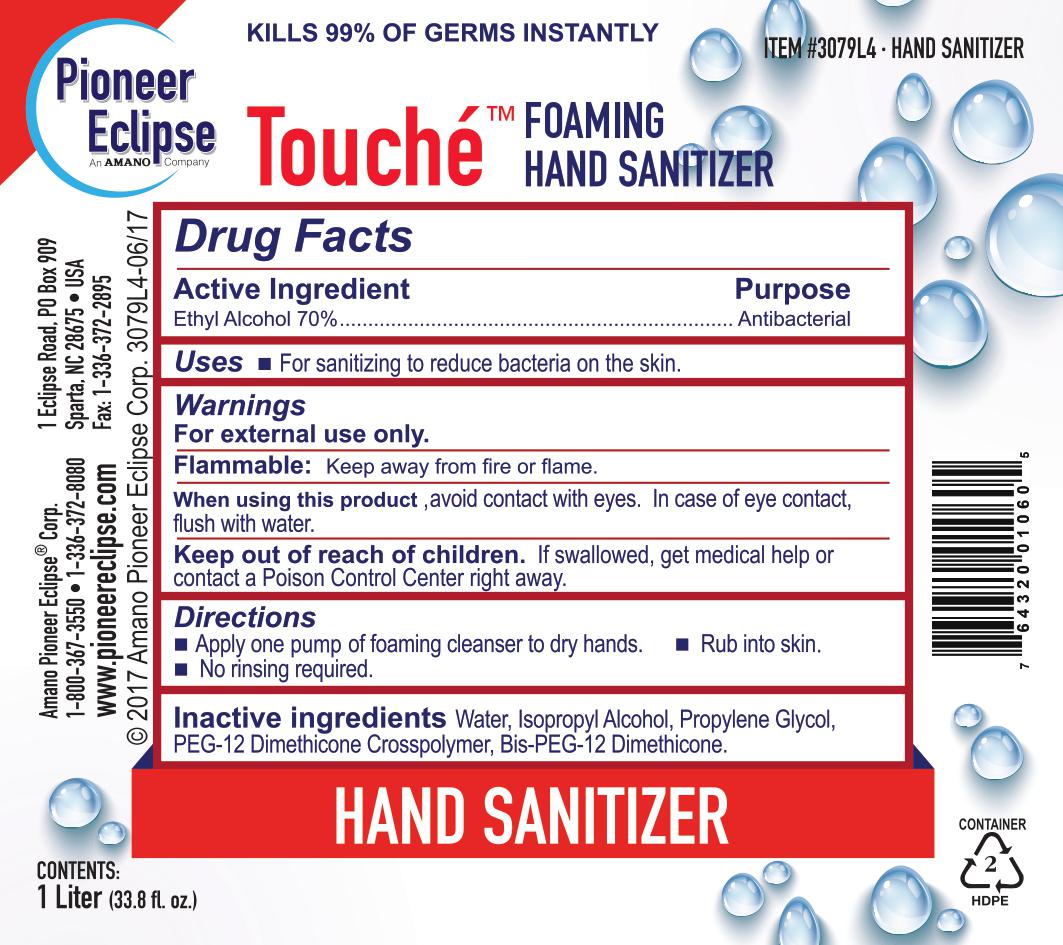 DRUG LABEL: Foaming Hand Sanitizer
NDC: 80401-112 | Form: LIQUID
Manufacturer: Uweport llc
Category: otc | Type: HUMAN OTC DRUG LABEL
Date: 20211230

ACTIVE INGREDIENTS: ALCOHOL 70 mL/100 mL
INACTIVE INGREDIENTS: 2-PHENYLPROPANAL PROPYLENE GLYCOL ACETAL 0.5 mL/100 mL; BIS-PEG-12 DIMETHICONE (500 MPA.S) 1.5 mL/100 mL; WATER; DIMETHICONE/DIENE DIMETHICONE CROSSPOLYMER 1 mL/100 mL; ISOPROPYL ALCOHOL 0.5 mL/100 mL

The hand sanitizer is manufactured using only the following United States Pharmacopoeia (USP) grade ingredients in the preparation of the product (percentage in final product formulation) consistent with World Health Organization (WHO) recommendations:

1. Alcohol (ethanol) (USP or Food Chemical Codex (FCC) grade) (70%, volume/volume (v/v)) in an aqueous solution denatured according to Alcohol and Tobacco Tax and Trade Bureau regulations in 27 CFR part 20.
2. Propylene Glycol (0.55% v/v).
3. Isopropyl Alcohol (0.5% v/v)
4. BIS-PEG-12 Dimethicone (1.5%)
5. PEG-12 Dimethicone Crosspolymer (1%)
6. Sterile distilled water or boiled cold water.

The firm does not add other active or inactive ingredients. Different or additional ingredients may impact the quality and potency of the product.

Active Ingredient(s)

Alcohol 70% v/v. Purpose: Antiseptic

Purpose

Antiseptic, Hand Sanitizer

Use

Hand Sanitizer to help reduce bacteria that potentially can cause disease. For use when soap and water are not available.

Warnings

For external use only. Flammable. Keep away from heat or flame

Do not use

- in children less than 2 months of age
- on open skin wounds

When using this product keep out of eyes, ears, and mouth. In case of contact with eyes, rinse eyes thoroughly with water.
Stop use and ask a doctor if irritation or rash occurs. These may be signs of a serious condition.
Keep out of reach of children. If swallowed, get medical help or contact a Poison Control Center right away.

Stop use and ask a doctor if irritation or rash occurs. These may be signs of a serious condition.

Keep out of reach of children. If swallowed, get medical help or contact a Poison Control Center right away.

Directions

- Place enough product on hands to cover all surfaces. Rub hands together until dry.
- Supervise children under 6 years of age when using this product to avoid swallowing.

Other information

- Store between 15-30C (59-86F)
- Avoid freezing and excessive heat above 40C (104F)

Inactive ingredients

Propylene Glycol, PEG-12 Dimethicone Crosspolymer, BIS-PEG-12 Dimethicone, purified water USP

Package Label - Principal Display Panel

1000 mL NDC:80401-101-11